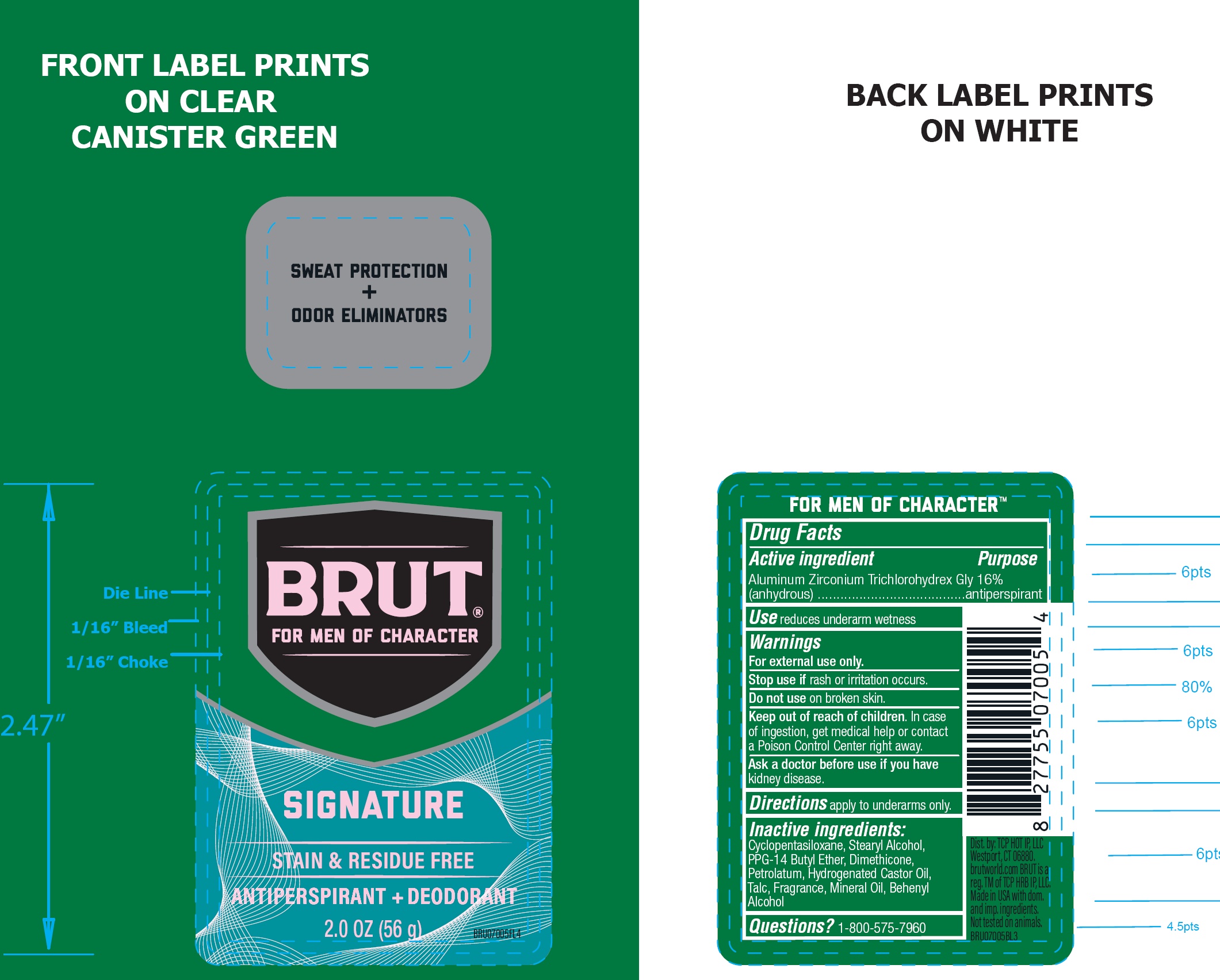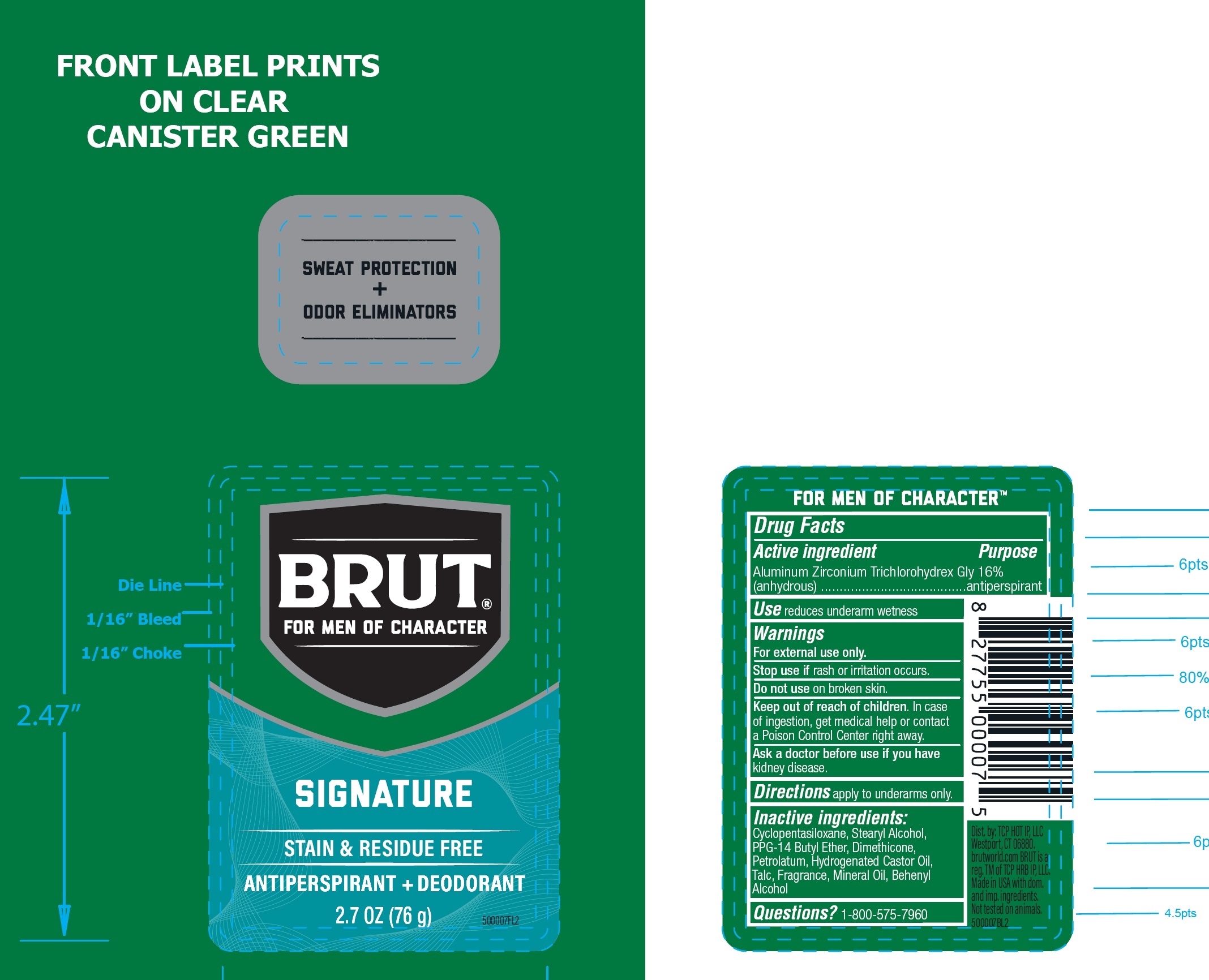 DRUG LABEL: Brut Signature Anti-Perspirant and Deodorant
NDC: 81277-001 | Form: STICK
Manufacturer: Sodalis USA LLC
Category: otc | Type: HUMAN OTC DRUG LABEL
Date: 20241108

ACTIVE INGREDIENTS: ALUMINUM ZIRCONIUM TRICHLOROHYDREX GLY 19 g/100 g
INACTIVE INGREDIENTS: CYCLOMETHICONE 5; STEARYL ALCOHOL; PPG-14 BUTYL ETHER; DIMETHICONE; PETROLATUM; HYDROGENATED CASTOR OIL; TALC; MINERAL OIL; DOCOSANOL

Brut Signature Anti-Perspirant and Deodorant

Active ingredient

Aluminum Zirconium Trichlorohydrex Gly 16% (anhydrous)

Purpose

antiperspirant

Use

reduces underarm wetness

Warnings

For external use only.

Stop use if

rash or irritation occurs.

Do not use

on broken skin.

Keep out of reach of children.

In case of ingestion, get medical help or contact a Poison Control Center right away.

Ask a doctor before use if you have

kidney disease.

Directions

apply to underarms only.

Inactive ingredients:

Cyclopentasiloxane, Stearyl Alcohol, PPG-14 Butyl Ether, Dimethicone, Petrolatum, Hydrogenated Castor Oil, Talc, Fragrance, Mineral Oil, Behenyl Alcohol

Questions?

1-800-575-7960